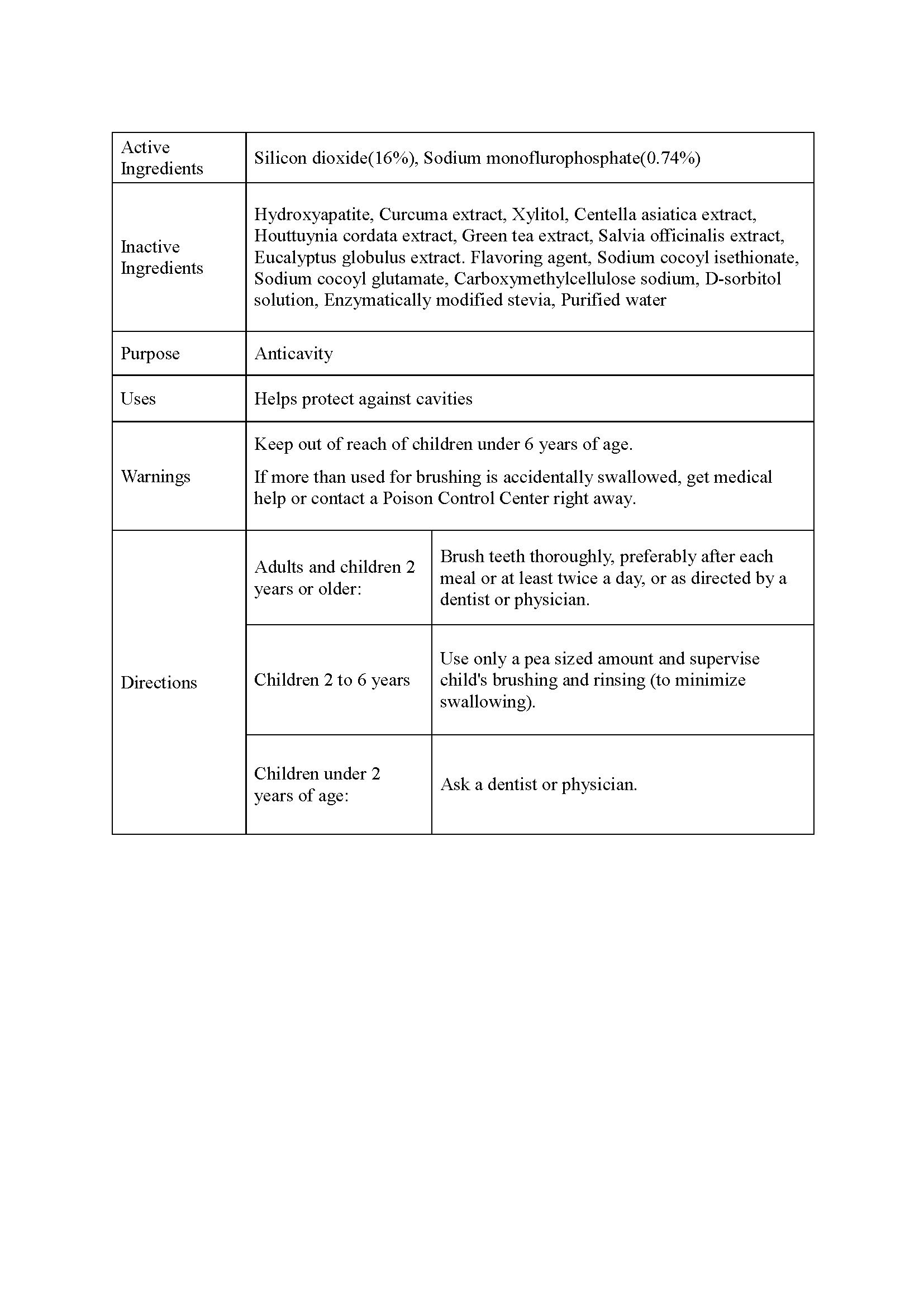 DRUG LABEL: Doctrust K
NDC: 76670-0003 | Form: LIQUID
Manufacturer: Dr.s Medi Co.,Ltd.
Category: otc | Type: HUMAN OTC DRUG LABEL
Date: 20210821

ACTIVE INGREDIENTS: SODIUM FLUORIDE 0.74 g/100 mL
INACTIVE INGREDIENTS: WATER

Drug Facts

ACTIVE INGREDIENT

sodium fluoride

INACTIVE INGREDIENT

Hydroxyapatite, Curcuma extract, Xylitol, Centella asiatica extract, Houttuynia cordata extract, Green tea extract, Salvia officinalis extract, Eucalyptus globulus extract. Flavoring agent, Sodium cocoyl isethionate, Sodium cocoyl glutamate, Carboxymethylcellulose sodium, D-sorbitol solution, Enzymatically modified stevia, Purified water

PURPOSE

Helps protect against cavities

KEEP OUT OF REACH OF THE CHILDREN

INDICATIONS AND USAGE

- Adults and children 2 years or older:

Brush teeth thoroughly, preferably after each meal or at least twice a day, or as directed by a dentist or physician

- Children 2 to 6 years

Use only a pea sized amount and supervise child's brushing and rinsing (to minimize swallowing).

- Children under 2 years of age:

Ask a dentist or physician.

Keep out of reach of children under 6 years of age.
If more than used for brushing is accidentally swallowed, get medical help or contact a Poison Control Center right away.

DOSAGE AND ADMINISTRATION

dental use only